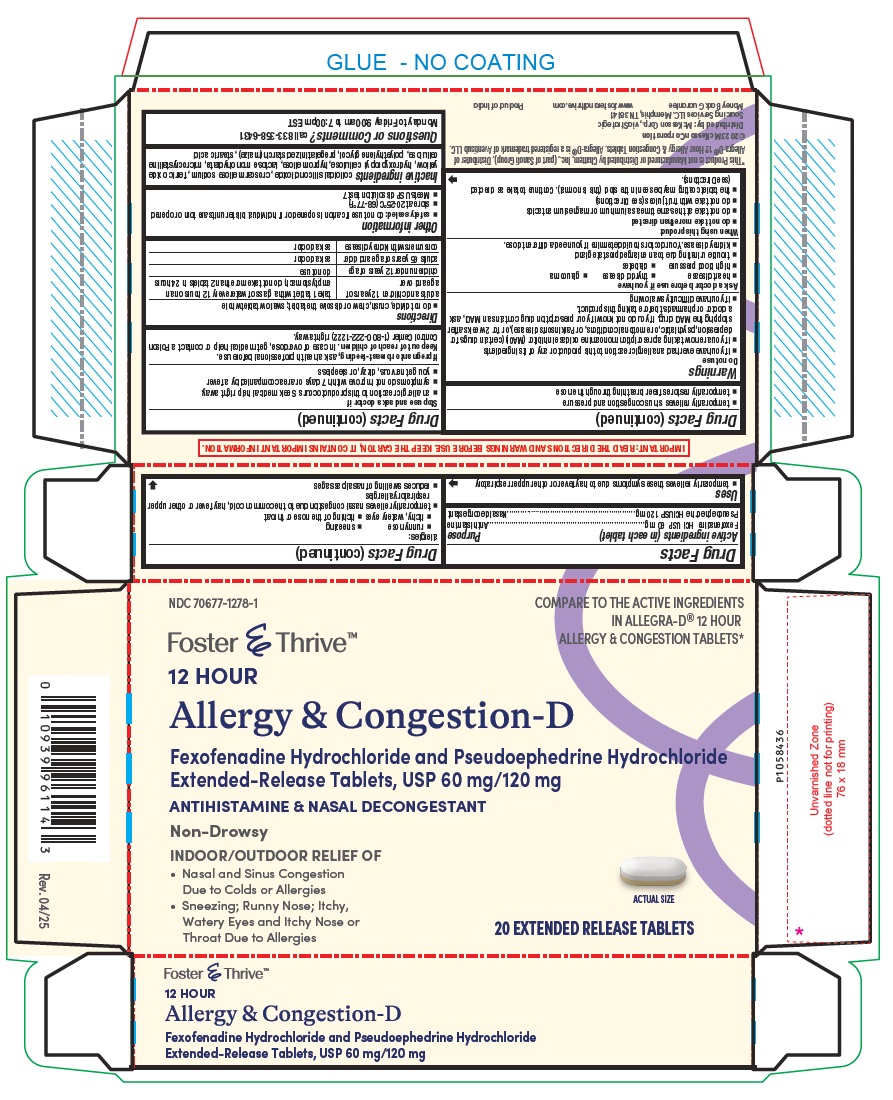 DRUG LABEL: Fexofenadine Hydrochloride and Pseudoephedrine Hydrochloride
NDC: 70677-1278 | Form: TABLET, FILM COATED, EXTENDED RELEASE
Manufacturer: Strategic Sourcing Services LLC
Category: otc | Type: Human OTC Drug Label
Date: 20250509

ACTIVE INGREDIENTS: FEXOFENADINE HYDROCHLORIDE 60 mg/1 1; PSEUDOEPHEDRINE HYDROCHLORIDE 120 mg/1 1
INACTIVE INGREDIENTS: SILICON DIOXIDE; CROSCARMELLOSE SODIUM; FERRIC OXIDE YELLOW; HYPROMELLOSE 2208 (100000 MPA.S); MICROCRYSTALLINE CELLULOSE; LACTOSE MONOHYDRATE; HYDROXYPROPYL CELLULOSE (110000 WAMW); POLYETHYLENE GLYCOL 6000; POLYETHYLENE GLYCOL 400; STARCH, CORN; STEARIC ACID

Fexofenadine Hydrochloride and Pseudoephedrine Hydrochloride Extended-Release Tablets USP

Drug Facts

Active ingredients (in each tablet)
Fexofenadine HCl USP 60 mg
Pseudoephedrine HCl USP 120 mg

Purpose

Antihistamine
Nasal decongestant

Uses

- temporarily relieves these symptoms due to hay fever or other upper respiratory allergies:
- runny nose
- sneezing
- itchy, watery eyes
- itching of the nose or throat
- temporarily relieves nasal congestion due to the common cold, hay fever or other upper respiratory allergies
- reduces swelling of nasal passages
- temporarily relieves sinus congestion and pressure
- temporarily restores freer breathing through the nose

Warnings

Do not use

- if you have ever had an allergic reaction to this product or any of its ingredients
- if you are now taking a prescription monoamine oxidase inhibitor (MAOI) (certain drugs for depression, psychiatric, or emotional conditions, or Parkinson’s disease), or for 2 weeks after stopping the MAOI drug. If you do not know if your prescription drug contains an MAOI, ask a doctor or pharmacist before taking this product.
- if you have difficulty swallowing

Ask a doctor before use if you have

- heart disease
- thyroid disease
- glaucoma
- high blood pressure
- diabetes
- trouble urinating due to an enlarged prostate gland
- kidney disease. Your doctor should determine if you need a different dose.

When using this product

- do not take more than directed
- do not take at the same time as aluminum or magnesium antacids
- do not take with fruit juices (see Directions)
- the tablet coating may be seen in the stool (this is normal). Continue to take as directed (see Directions).

Stop use and ask a doctor if

- an allergic reaction to this product occurs. Seek medical help right away.
- symptoms do not improve within 7 days or are accompanied by a fever
- you get nervous, dizzy, or sleepless

PREGNANCY OR BREAST FEEDING

If pregnant or breast-feeding, ask a health professional before use.

Keep out of reach of children.

In case of overdose, get medical help or contact a Poison Control Center (1-800-222-1222) right away.

Directions

- do not divide, crush, chew or dissolve the tablet; swallow tablet whole

adults and children 12 years of age and over | take 1 tablet with a glass of water every 12 hours on an empty stomach; do not take more than 2 tablets in 24 hours
children under 12 years of age | do not use
adults 65 years of age and older | ask a doctor
consumers with kidney disease | ask a doctor

Other information

- safety sealed: do not use if carton is opened or if individual blister units are torn or opened
- store at 20-25°C (68-77°F).
- Meets USP dissolution test 7

Inactive ingredients

colloidal silicon dioxide, croscarmellose sodium, ferric oxide yellow, hydroxypropyl cellulose, hypromellose, lactose monohydrate, microcrystalline cellulose, polyethylene glycol, pregelatinized starch (maize), stearic acid
Questions or Comments?
call 833-358-6431 Monday to Friday 9:00am to 7:00pm EST

IMPORTANT: READ THE DIRECTIONS AND WARNINGS BEFORE USE. KEEP THE CARTON, IT CONTAINS IMPORTANT INFORMATION.

©2023 McKesson Corporation

Distributed by: McKesson Corp., via Strategic
Sourcing Services LLC. Memphis, TN 38141

www.fosterandthrive.com

Product of India

Rev. 04/25

PACKAGE LABEL-PRINCIPAL DISPLAY PANEL - 2 x 10 Blister Carton

NDC 70677-1278-1

Foster ξ Thrive™

12 HOUR

COMPARE TO THE ACTIVE INGREDIENTS
IN ALLEGRA-D® 12 HOUR
ALLERGY & CONGESTION TABLETS*
Allergy & Congestion-D

Fexofenadine Hydrochloride and Pseudoephedrine Hydrochloride
Extended-Release Tablets, USP 60 mg/120 mg

ANTIHISTAMINE & NASAL DECONGESTANT
Non-Drowsy

INDOOR / OUTDOOR RELIEF OF

• Nasal and Sinus Congestion

Due to Colds or Allergies

• Sneezing; Runny Nose; Itchy,

Watery Eyes and Itchy Nose or

Throat Due to Allergies

ACTUAL SIZE

20 EXTENDED RELEASE TABLETS